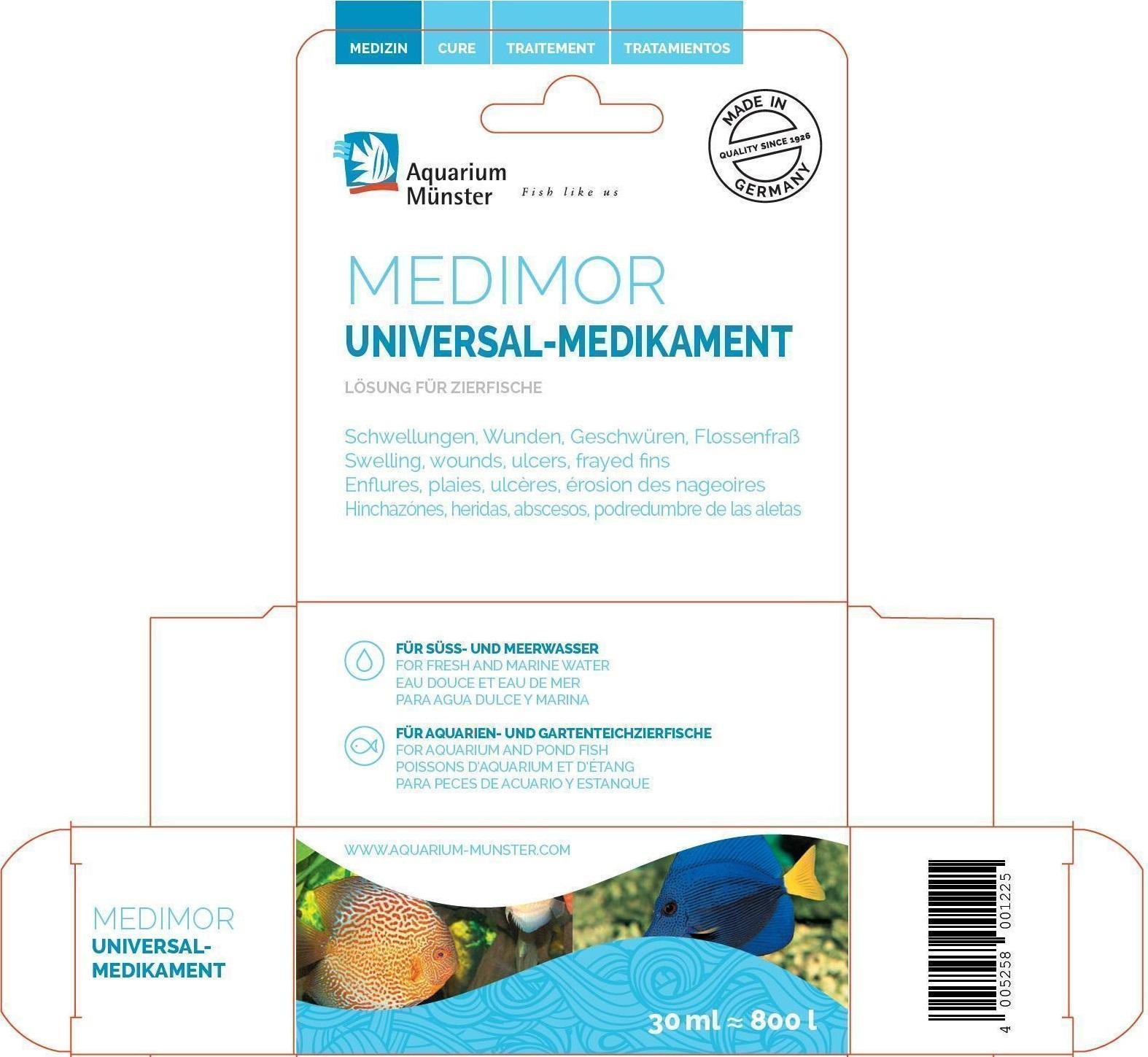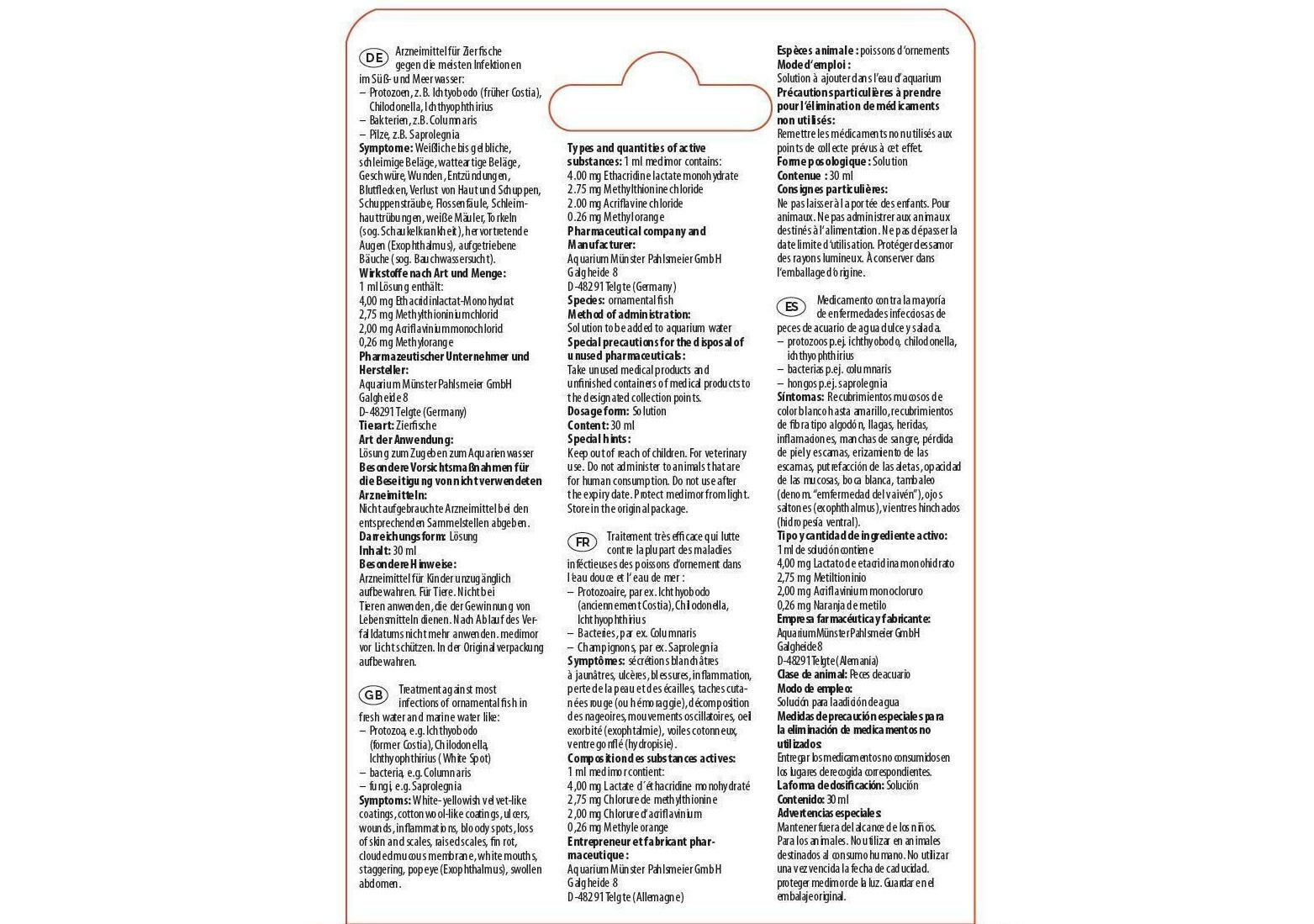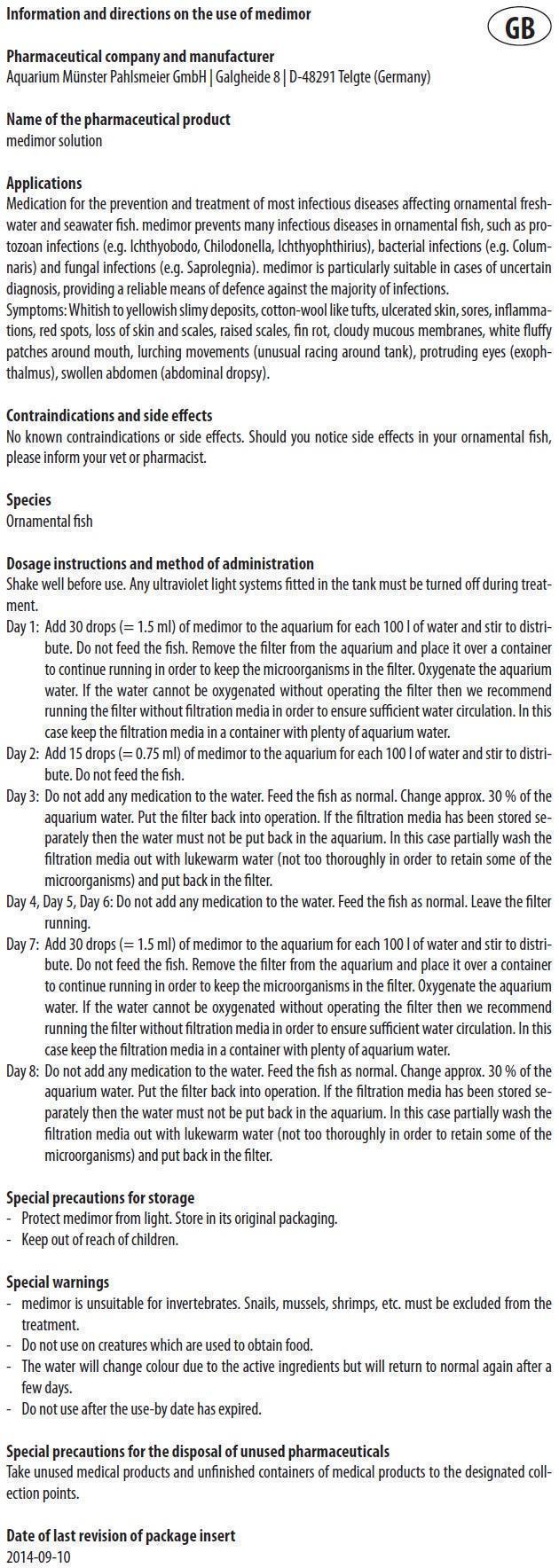 DRUG LABEL: MEDIMOR
NDC: 86052-004 | Form: SOLUTION
Manufacturer: Aquarium Muenster Pahlsmeier GmbH
Category: animal | Type: OTC ANIMAL DRUG LABEL
Date: 20240427

ACTIVE INGREDIENTS: ETHACRIDINE LACTATE 4 mg/1 mL; METHYLENE BLUE ANHYDROUS 2.75 mg/1 mL; ACRIFLAVINE HYDROCHLORIDE 2 mg/1 mL; METHYL ORANGE 0.26 mg/1 mL

MEDIMOR

Information and directions on the use of medimor

Pharmaceutical company and manufacturer
Aquarium Münster Pahlsmeier GmbH | Galgheide 8 | D-48291 Telgte (Germany)

Name of the pharmaceutical product
medimor solution

Applications

Medication for the prevention and treatment of most infectious diseases affecting ornamental freshwater and seawater fish. medimor prevents many infectious diseases in ornamental fish, such as protozoan infections (e.g. Ichthyobodo, Chilodonella, Ichthyophthirius), bacterial infections (e.g. Columnaris) and fungal infections (e.g. Saprolegnia). medimor is particularly suitable in cases of uncertain
diagnosis, providing a reliable means of defence against the majority of infections. Symptoms: Whitish to yellowish slimy deposits, cotton-wool like tufts, ulcerated skin, sores, inflammations, red spots, loss of skin and scales, raised scales, fin rot, cloudy mucous membranes, white fluffy patches around mouth, lurching movements (unusual racing around tank), protruding eyes (exophthalmus),
swollen abdomen (abdominal dropsy).

Types and quantities of active substances:

1 ml medimor contains:

4.00 mg Ethacridine lactate monohydrate

2.75 mg Methylthionine chloride

2.00 mg Acriflavine chloride

0.26 mg Methyl orange

Contraindications and side effects

No known contraindications or side effects. Should you notice side effects in your ornamental fish, please inform your vet or pharmacist.

Species

Ornamental fish

Dosage instructions and method of administration

Shake well before use. Any ultraviolet light systems fitted in the tank must be turned off during treatment.
Day 1: Add 30 drops (= 1.5 ml) of medimor to the aquarium for each 100 l of water and stir to distribute. Do not feed the fish. Remove the filter from the aquarium and place it over a container to continue running in order to keep the microorganisms in the filter. Oxygenate the aquarium water. If the water cannot be oxygenated without operating the filter then we recommend running the filter without filtration media in order to ensure sufficient water circulation. In this case keep the filtration media in a container with plenty of aquarium water.
Day 2: Add 15 drops (= 0.75 ml) of medimor to the aquarium for each 100 l of water and stir to distribute. Do not feed the fish.
Day 3: Do not add any medication to the water. Feed the fish as normal. Change approx. 30 % of the aquarium water. Put the filter back into operation. If the filtration media has been stored separately then the water must not be put back in the aquarium. In this case partially wash the filtration media out with lukewarm water (not too thoroughly in order to retain some of the microorganisms) and put back in the filter.
Day 4, Day 5, Day 6: Do not add any medication to the water. Feed the fish as normal. Leave the filter running.
Day 7: Add 30 drops (= 1.5 ml) of medimor to the aquarium for each 100 l of water and stir to distribute. Do not feed the fish. Remove the filter from the aquarium and place it over a container to continue running in order to keep the microorganisms in the filter. Oxygenate the aquarium water. If the water cannot be oxygenated without operating the filter then we recommend running the filter without filtration media in order to ensure sufficient water circulation. In this case keep the filtration media in a container with plenty of aquarium water.
Day 8: Do not add any medication to the water. Feed the fish as normal. Change approx. 30 % of the aquarium water. Put the filter back into operation. If the filtration media has been stored separately then the water must not be put back in the aquarium. In this case partially wash the filtration media out with lukewarm water (not too thoroughly in order to retain some of the microorganisms) and put back in the filter.

Special precautions for storage

- Protect medimor from light. Store in its original packaging.

- Keep out of reach of children.

Special warnings

- medimor is unsuitable for invertebrates. Snails, mussels, shrimps, etc. must be excluded from the treatment.
- Do not use on creatures which are used to obtain food.
- The water will change colour due to the active ingredients but will return to normal again after a few days.
- Do not use after the use-by date has expired.

Special precautions for the disposal of unused pharmaceuticals

Take unused medical products and unfinished containers of medical products to the designated collection points.

Date of last revision of package insert
2014-09-10